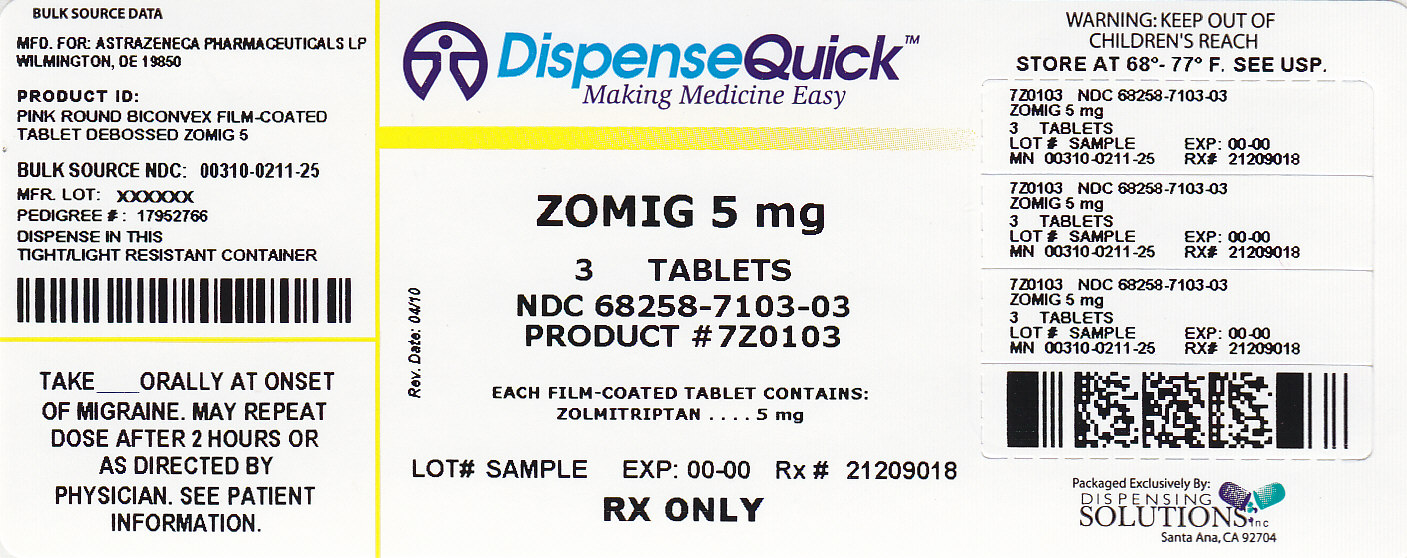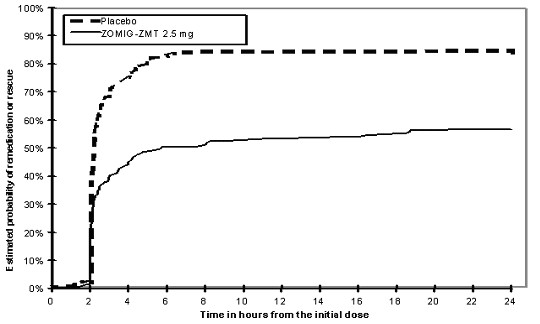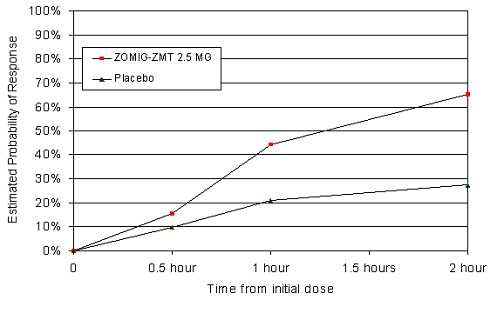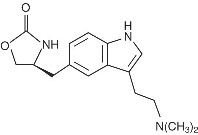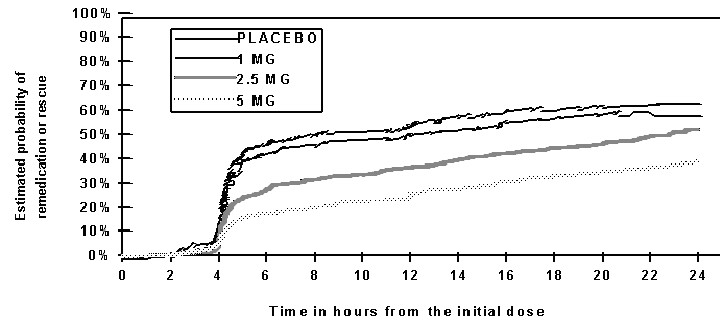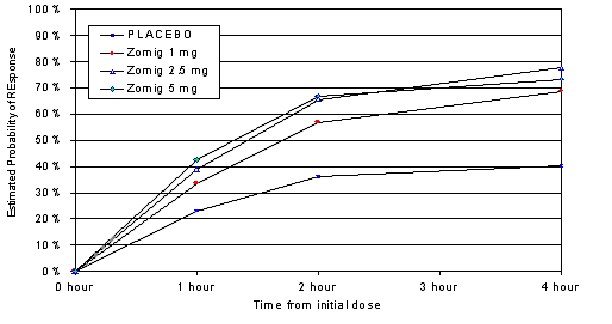 DRUG LABEL: ZOMIG
NDC: 68258-7103 | Form: TABLET
Manufacturer: Dispensing Solutions, Inc.
Category: prescription | Type: HUMAN PRESCRIPTION DRUG LABEL
Date: 20111010

ACTIVE INGREDIENTS: ZOLMITRIPTAN 5 mg/1 1
INACTIVE INGREDIENTS: ANHYDROUS LACTOSE; CELLULOSE, MICROCRYSTALLINE; SODIUM STARCH GLYCOLATE TYPE A POTATO; MAGNESIUM STEARATE; HYDROXYPROPYL CELLULOSE; TITANIUM DIOXIDE; POLYETHYLENE GLYCOL 400; POLYETHYLENE GLYCOL 8000; FERRIC OXIDE RED

ZOMIG®
(zolmitriptan)
TABLETS
ZOMIG-ZMT®
(zolmitriptan)
ORALLY DISINTEGRATING TABLETS

DESCRIPTION

ZOMIG® (zolmitriptan) Tablets and ZOMIG-ZMT® (zolmitriptan) Orally Disintegrating Tablets contain zolmitriptan, which is a selective 5-hydroxytryptamine 1B/1D (5-HT1B/1D) receptor agonist. Zolmitriptan is chemically designated as (S)-4-[[3-[2-(dimethylamino)ethyl]-1H-indol-5-yl]methyl]-2-oxazolidinone and has the following chemical structure:

The empirical formula is C16H21N3O2, representing a molecular weight of 287.36. Zolmitriptan is a white to almost white powder that is readily soluble in water. ZOMIG Tablets are available as 2.5 mg (yellow) and 5 mg (pink) film coated tablets for oral administration. The film coated tablets contain anhydrous lactose NF, microcrystalline cellulose NF, sodium starch glycolate NF, magnesium stearate NF, hydroxypropyl methylcellulose USP, titanium dioxide USP, polyethylene glycol 400 NF, yellow iron oxide NF (2.5 mg tablet), red iron oxide NF (5 mg tablet), and polyethylene glycol 8000 NF.

ZOMIG-ZMT® Orally Disintegrating Tablets are available as 2.5 mg and 5.0 mg white uncoated tablets for oral administration. The orally disintegrating tablets contain mannitol USP, microcrystalline cellulose NF, crospovidone NF, aspartame NF, sodium bicarbonate USP, citric acid anhydrous USP, colloidal silicon dioxide NF, magnesium stearate NF and orange flavor SN 027512.

CLINICAL PHARMACOLOGY

Mechanism of Action:

Zolmitriptan binds with high affinity to human recombinant 5-HT1D and 5-HT1B receptors. Zolmitriptan exhibits modest affinity for 5-HT1A receptors, but has no significant affinity (as measured by radioligand binding assays) or pharmacological activity at 5-HT2, 5-HT3, 5-HT4, alpha1-, alpha2-, or beta1- adrenergic; H1, H2, histaminic; muscarinic; dopamine1, or dopamine2 receptors. The N-desmethyl metabolite also has high affinity for 5-HT1B/1D and modest affinity for 5-HT1A receptors.

Current theories proposed to explain the etiology of migraine headache suggest that symptoms are due to local cranial vasodilatation and/or to the release of sensory neuropeptides (vasoactive intestinal peptide, substance P and calcitonin gene-related peptide) through nerve endings in the trigeminal system. The therapeutic activity of zolmitriptan for the treatment of migraine headache can most likely be attributed to the agonist effects at the 5-HT1B/1D receptors on intracranial blood vessels (including the arterio-venous anastomoses) and sensory nerves of the trigeminal system which result in cranial vessel constriction and inhibition of pro-inflammatory neuropeptide release.

Clinical Pharmacokinetics and Bioavailability

Absorption:

Zolmitriptan is well absorbed after oral administration for both the conventional tablets and the orally disintegrating tablets. Zolmitriptan displays linear kinetics over the dose range of 2.5 to 50 mg.

The AUC and Cmax of zolmitriptan are similar following administration of ZOMIG Tablets and ZOMIG-ZMT Orally Disintegrating Tablets, but the Tmax is somewhat later with ZOMIG-ZMT, with a median Tmax of 3 hours for the orally disintegrating tablet compared with 1.5 hours for the conventional tablet. The AUC, Cmax,and Tmax for the active N-desmethyl metabolite are similar for the two formulations.

During a moderate to severe migraine attack, mean AUC0-4 and Cmax for zolmitriptan, dosed as a conventional tablet, were decreased by 40% and 25%, respectively, and mean Tmax was delayed by one-half hour compared to the same patients during a migraine free period.

Food has no significant effect on the bioavailability of zolmitriptan. No accumulation occurred on multiple dosing.

Distribution:

Mean absolute bioavailability is approximately 40%. The mean apparent volume of distribution is 7.0 L/kg. Plasma protein binding of zolmitriptan is 25% over the concentration range of 10- 1000ng/mL.

Metabolism:

Zolmitriptan is converted to an active N-desmethyl metabolite such that the metabolite concentrations are about two-thirds that of zolmitriptan. Because the 5HT1B/1D potency of the metabolite is 2 to 6 times that of the parent, the metabolite may contribute a substantial portion of the overall effect after zolmitriptan administration.

Elimination:

Total radioactivity recovered in urine and feces was 65% and 30% of the administered dose, respectively. About 8% of the dose was recovered in the urine as unchanged zolmitriptan. Indole acetic acid metabolite accounted for 31% of the dose, followed by N-oxide (7%) and N-desmethyl (4%) metabolites. The indole acetic acid and N-oxide metabolites are inactive.

Mean total plasma clearance is 31.5mL/min/kg, of which one-sixth is renal clearance. The renal clearance is greater than the glomerular filtration rate suggesting renal tubular secretion.

Special Populations:

Age: Zolmitriptan pharmacokinetics in healthy elderly non-migraineur volunteers (age 65−76 yrs) were similar to those in younger non-migraineur volunteers (age 18 - 39 yrs).

Gender: Mean plasma concentrations of zolmitriptan were up to 1.5-fold higher in females than males.

Renal Impairment: Clearance of zolmitriptan was reduced by 25% in patients with severe renal impairment (Clcr ≥ 5 ≤ 25 mL/min) compared to the normal group (Clcr > = 70 mL/min); no significant change in clearance was observed in the moderately renally impaired group (Clcr ≥ 26 ≤ 50 mL/min).

Hepatic Impairment: In severely hepatically impaired patients, the mean Cmax, Tmax, and AUC0-∞ of zolmitriptan were increased 1.5, 2 (2 vs 4 hr), and 3-fold, respectively, compared to normals. Seven out of 27 patients experienced 20 to 80 mm Hg elevations in systolic and/or diastolic blood pressure after a 10 mg dose. Zolmitriptan should be administered with caution in subjects with liver disease, generally using doses less than 2.5 mg (see WARNINGS and PRECAUTIONS).

Hypertensive Patients: No differences in the pharmacokinetics of zolmitriptan or its effects on blood pressure were seen in mild to moderate hypertensive volunteers compared to normotensive controls.

Race:: Retrospective analysis of pharmacokinetic data between Japanese and Caucasians revealed no significant differences.

Drug Interactions:

All drug interaction studies were performed in healthy volunteers using a single 10 mg dose of zolmitriptan and a single dose of the other drug except where otherwise noted.

Fluoxetine: The pharmacokinetics of zolmitriptan, as well as its effect on blood pressure, were unaffected by 4 weeks of pretreatment with oral fluoxetine (20 mg/day).

MAO Inhibitors: Following one week of administration of 150 mg bid moclobemide, a specific MAO-A inhibitor, there was an increase of about 25% in both Cmax and AUC for zolmitriptan and a 3-fold increase in the Cmax and AUC of the active N-desmethyl metabolite of zolmitriptan (see CONTRAINDICATIONS and PRECAUTIONS).

Selegiline, a selective MAO-B inhibitor, at a dose of 10 mg/day for 1 week, had no effect on the pharmacokinetics of zolmitriptan and its metabolite.

Propranolol: Cmax and AUC of zolmitriptan increased 1.5-fold after one week of dosing with propranolol (160 mg/day). Cmax and AUC of the N-desmethyl metabolite were reduced by 30% and 15%, respectively. There were no interactive effects on blood pressure or pulse rate following administration of propranolol with zolmitriptan.

Acetaminophen: A single 1 g dose of acetaminophen does not alter the pharmacokinetics of zolmitriptan and its N-desmethyl metabolite. However, zolmitriptan delayed the Tmax of acetaminophen by one hour.

Metoclopramide: A single 10 mg dose of metoclopramide had no effect on the pharmacokinetics of zolmitriptan or its metabolites.

Oral Contraceptives: Retrospective analysis of pharmacokinetic data across studies indicated that mean plasma concentrations of zolmitriptan were generally higher in females taking oral contraceptives compared to those not taking oral contraceptives. Mean Cmax and AUC of zolmitriptan were found to be higher by 30% and 50%, respectively, and Tmax was delayed by one-half hour in females taking oral contraceptives. The effect of zolmitriptan on the pharmacokinetics of oral contraceptives has not been studied.

Cimetidine: Following the administration of cimetidine, the half-life and AUC of a 5 mg dose of zolmitriptan and its active metabolite were approximately doubled (see PRECAUTIONS).

Clinical Studies:

The efficacy of ZOMIG Tablets in the acute treatment of migraine headaches was demonstrated in five randomized, double-blind, placebo controlled studies, of which 2 utilized the 1 mg dose, 2 utilized the 2.5 mg dose and 4 utilized the 5 mg dose; all studies used the marketed formulation. In study 1, patients treated their headaches in a clinic setting. In the other studies, patients treated their headaches as outpatients. In study 4, patients who had previously used sumatriptan were excluded, whereas in the other studies no such exclusion was applied. Patients enrolled in these 5 studies were predominantly female (82%) and Caucasian (97%) with a mean age of 40 years (range 12-65). Patients were instructed to treat a moderate to severe headache. Headache response, defined as a reduction in headache severity from moderate or severe pain to mild or no pain, was assessed at 1, 2, and, in most studies, 4 hours after dosing. Associated symptoms such as nausea, photophobia, and phonophobia were also assessed. Maintenance of response was assessed for up to 24 hours postdose. A second dose of ZOMIG Tablets or other medication was allowed 2 to 24 hours after the initial treatment for persistent and recurrent headache. The frequency and time to use of these additional treatments were also recorded. In all studies, the effect of zolmitriptan was compared to placebo in the treatment of a single migraine attack.

In all five studies, the percentage of patients achieving headache response 2 hours after treatment was significantly greater among patients receiving ZOMIG Tablets at all doses (except for the 1 mg dose in the smallest study) compared to those who received placebo. In the two studies that evaluated the 1 mg dose, there was a statistically significant greater percentage of patients with headache response at 2 hours in the higher dose groups (2.5 and/or 5 mg) compared to the 1 mg dose group. There were no statistically significant differences between the 2.5 and 5 mg dose groups (or of doses up to 20 mg) for the primary end point of headache response at 2 hours in any study. The results of these controlled clinical studies are summarized in Table 1.

Comparisons of drug performance based upon results obtained in different clinical trials are never reliable. Because studies are conducted at different times, with different samples of patients, by different investigators, employing different criteria and/or different interpretations of the same criteria, under different conditions (dose, dosing regimen, etc.), quantitative estimates of treatment response and the timing of response may be expected to vary considerably from study to study.

Table 1: Percentage of Patients with Headache Response (Mild or no Headache) 2 Hours Following Treatment (n=number of patients randomized).
 | Placebo | ZOMIG; 1.0 mg | ZOMIG; 2.5 mg | ZOMIG; 5 mg
Study 1 | 16%; (n=19) | 27%; (n=22) | NA [NA - not applicable] | 60% [p<0.05 in comparison with placebo.] [p<0.05 in comparison with 1 mg.]; (n=20)
Study 2 | 19%; (n=88) | NA | NA | 66%; (n=179)
Study 3 | 34%; (n=121) | 50%; (n=140) | 65%; (n=260) | 67%; (n=245)
Study 4 | 44%; (n=55) | NA | NA | 59%; (n=491)
Study 5 | 36%; (n=92) | NA; NA | 62%; (n=178) | NA

The estimated probability of achieving an initial headache response by 4 hours following treatment is depicted in Figure 1.

Figure 1: Estimated Probability Of Achieving Initial Headache ResponseWithin 4 Hours*

*Figure 1 shows the Kaplan-Meier plot of the probability over time of obtaining headache response (no or mild pain) following treatment with zolmitriptan. The averages displayed are based on pooled data from 3 placebo controlled, outpatient trials providing evidence of efficacy (Trials 2, 3 and 5). Patients not achieving headache response or taking additional treatment prior to 4 hours were censored at 4 hours.

For patients with migraine associated photophobia, phonophobia, and nausea at baseline, there was a decreased incidence of these symptoms following administration of ZOMIG as compared to placebo.

Two to 24 hours following the initial dose of study treatment, patients were allowed to use additional treatment for pain relief in the form of a second dose of study treatment or other medication. The estimated probability of patients taking a second dose or other medication for migraine over the 24 hours following the initial dose of study treatment is summarized in Figure 2.

Figure 2: The Estimated Probability Of Patients Taking A Second Dose Or Other Medication For Migraines Over The 24 Hours Following The Initial Dose Of Study Treatment*

*This Kaplan-Meier plot is based on data obtained in 3 placebo controlled clinical trials (Study 2, 3 and 5). Patients not using additional treatments were censored at 24 hours. The plot includes both patients who had headache response at 2 hours and those who had no response to the initial dose. It should be noted that the protocols did not allow remedication within 2 hours postdose.

The efficacy of ZOMIG was unaffected by presence of aura; duration of headache prior to treatment; relationship to menses; gender, age, or weight of the patient; pretreatment nausea, or concomitant use of common migraine prophylactic drugs.

ZOMIG-ZMT Orally Disintegrating Tablets

The efficacy of ZOMIG-ZMT 2.5 mg was demonstrated in a randomized, placebo-controlled trial that was similar in design to the trials of ZOMIG Tablets. Patients were instructed to treat a moderate to severe headache. Of the 471 patients treated in the study, 87% were female and 97% were Caucasian, with a mean age of 41 years (range 18-62). At 2 hours post-dosing response rates in patients treated with ZOMIG-ZMT 2.5 mg were 63% compared to 22% in the placebo group. The difference was statistically significant. The estimated probability of achieving an initial headache response by 2 hours following treatment with ZOMIG-ZMT Tablets is depicted in Figure 3.

Figure 3: Estimated Probability of Achieving Initial Headache Response by 2 Hours

Figure 3 shows the Kaplan-Meier plot of the probability over time of obtaining headache response (no or mild pain) following treatment with ZOMIG-ZMT Tablets or placebo. Patients taking additional treatment or not achieving headache response prior to 2 hours were censored at 2 hours.

For patients with migraine-associated photophobia, phonophobia and nausea at baseline, there was a decreased incidence of these symptoms following administration of ZOMIG-ZMT as compared to placebo.

Two to 24 hours following the initial dose of study treatment, patients were allowed to use additional treatment in the form of a second dose of study treatment or other medication. The estimated probability of patients taking a second dose or other medication for migraine over the 24 hours following the initial dose of study treatment is summarized in Figure 4.

Figure 4: The Estimated Probability of Patients Taking a Second Dose or Other Medication for Migraines Over the 24 Hours Following The Initial Dose of Study Treatment

In this Kaplan-Meier plot, patients not using additional treatments were censored at 24 hours. The plot includes both patients who had headache response at 2 hours and those who had no response to the initial dose. Remedication was allowed 2 hours post-dose, and unlike the conventional tablet, remedication prior to 4 hours was not discouraged.

INDICATIONS AND USAGE

ZOMIG is indicated for the acute treatment of migraine with or without aura in adults.

ZOMIG should only be used where a clear diagnosis of migraine has been established.

ZOMIG is not intended for the prophylactic therapy of migraine or for use in the management of hemiplegic or basilar migraine (see CONTRAINDICATIONS). Safety and effectiveness of ZOMIG have not been established for cluster headache, which is present in an older, predominantly male population.

CONTRAINDICATIONS

ZOMIG should not be given to patients with ischemic heart disease (angina pectoris, history of myocardial infarction, or documented silent ischemia) or to patients who have symptoms or findings consistent with ischemic heart disease, coronary artery vasospasm, including Prinzmetal’s variant angina, or other significant underlying cardiovascular disease (see WARNINGS and PRECAUTIONS).

ZOMIG should not be given to patients with cerebrovascular syndromes including (but not limited to) stroke of any type as well as transient ischemic attacks (see WARNINGS).

ZOMIG should not be given to patients with peripheral vascular disease including (but not limited to) ischemic bowel disease (see WARNINGS and PRECAUTIONS).

Because ZOMIG may increase blood pressure, it should not be given to patients with uncontrolled hypertension (see WARNINGS).

ZOMIG should not be used within 24 hours of treatment with another 5-HT 1 agonist, or an ergotamine-containing or ergot-type medication like dihydroergotamine or methysergide.

ZOMIG should not be administered to patients with hemiplegic or basilar migraine.

Concurrent administration of MAO-A inhibitors or use of zolmitriptan within 2 weeks of discontinuation of MAO-A inhibitor therapy is contraindicated (see CLINICAL PHARMACOLOGY: Drug Interactions and PRECAUTIONS: Drug Interactions).

ZOMIG is contraindicated in patients who are hypersensitive to zolmitriptan or any of its inactive ingredients.

WARNINGS

Risk of Myocardial Ischemia and/or Infarction and Other Adverse Cardiac Events: ZOMIG should not be given to patients with documented ischemic or vasospastic coronary artery disease (see CONTRAINDICATIONS). It is strongly recommended that zolmitriptan not be given to patients in whom unrecognized coronary artery disease (CAD) is predicted by the presence of risk factors (e.g., hypertension, hypercholesterolemia, smoker, obesity, diabetes, strong family history of CAD, female with surgical or physiological menopause, or male over 40 years of age) unless a cardiovascular evaluation provides satisfactory clinical evidence that the patient is reasonably free of coronary artery and ischemic myocardial disease or other significant underlying cardiovascular disease. The sensitivity of cardiac diagnostic procedures to detect cardiovascular disease or predisposition to coronary artery vasospasm is modest, at best. If, during the cardiovascular evaluation, the patient’s medical history, electrocardiographic or other investigations reveal findings indicative of, or consistent with, coronary artery vasospasm or myocardial ischemia, zolmitriptan should not be administered (see CONTRAINDICATIONS). For patients with risk factors predictive of CAD, who are determined to have a satisfactory cardiovascular evaluation, it is strongly recommended that administration of the first dose of zolmitriptan take place in the setting of a physician’s office or similar medically staffed and equipped facility unless the patient has previously received zolmitriptan. Because cardiac ischemia can occur in the absence of clinical symptoms, consideration should be given to obtaining on the first occasion of use an electrocardiogram (ECG) during the interval immediately following ZOMIG, in these patients with risk factors.

It is recommended that patients who are intermittent long-term users of ZOMIG and who have or acquire risk factors predictive of CAD, as described above, undergo periodic interval cardiovascular evaluation as they continue to use ZOMIG.

The systematic approach described above is intended to reduce the likelihood that patients with unrecognized cardiovascular disease will be inadvertently exposed to zolmitriptan.

Cardiac Events and Fatalities:

Serious adverse cardiac events, including acute myocardial infarction, have been reported within a few hours following administration of zolmitriptan. Life-threatening disturbances of cardiac rhythm, and death have been reported within a few hours following the administration of other 5-HT1 agonists. Considering the extent of use of 5-HT1 agonists in patients with migraine, the incidence of these events is extremely low.

ZOMIG can cause coronary vasospasm; at least one of these events occurred in a patient with no cardiac disease history and with documented absence of coronary artery disease. Because of the close proximity of the events to ZOMIG use, a causal relationship cannot be excluded. In the cases where there has been known underlying coronary artery disease, the relationship is uncertain.

Patients with symptomatic Wolff-Parkinson-White syndrome or arrhythmias associated with other cardiac accessory conduction pathway disorders should not receive ZOMIG.

Premarketing experience with zolmitriptan:

Among the more than 2,500 patients with migraine who participated in premarketing controlled clinical trials of ZOMIG Tablets, no deaths or serious cardiac events were reported.

Postmarketing experience with zolmitriptan:

Serious cardiovascular events have been reported in association with the use of ZOMIG Tablets, and in very rare cases, these events have occurred in the absence of known cardiovascular disease. The uncontrolled nature of postmarketing surveillance, however, makes it impossible to determine definitively the proportion of the reported cases that were actually caused by zolmitriptan or to reliably assess causation in individual cases.

Cerebrovascular Events and Fatalities with 5-HT 1 agonists:

Cerebral hemorrhage, subarachnoid hemorrhage, stroke, and other cerebrovascular events have been reported in patients treated with 5-HT1 agonists; and some have resulted in fatalities. In a number of cases, it appears possible that the cerebrovascular events were primary, the agonist having been administered in the incorrect belief that the symptoms experienced were a consequence of migraine, when they were not. It should be noted that patients with migraine may be at increased risk of certain cerebrovascular events (e.g., stroke, hemorrhage, transient ischemic attack). (See CONTRAINDICATIONS.)

Serotonin Syndrome:

The development of a potentially life-threatening serotonin syndrome may occur with triptans, including ZOMIG treatment, particularly during combined use with selective serotonin reuptake inhibitors (SSRIs) or serotonin norepinephrine reuptake inhibitors (SNRIs). If concomitant treatment with ZOMIG and an SSRI (e.g. fluoxetine, paroxetine, sertraline, fluvoxamine, citalopram, escitalopram) or SNRI (e.g., venlafaxine, duloxetine) is clinically warranted, careful observation of the patient is advised, particularly during treatment initiation and dose increases. Serotonin syndrome symptoms may include mental status changes (e.g., agitation, hallucinations, coma), autonomic instability (e.g., tachycardia, labile blood pressure, hyperthermia), neuromuscular aberrations (e.g. hyperreflexia, incoordination) and/or gastrointestinal symptoms (e.g. nausea, vomiting, diarrhea). (See PRECAUTIONS, Drug Interactions).

Other Vasospasm-Related Events:

5-HT1 agonists may cause vasospastic reactions other than coronary artery vasospasm such as peripheral and gastrointestinal vascular ischemia. As with other serotonin 5HT1 agonists, very rare gastrointestinal ischemic events including ischemic colitis and gastrointestinal infarction or necrosis have been reported with ZOMIG Tablets; these may present as bloody diarrhea or abdominal pain. (See CONTRAINDICATIONS.)

Very rare reports of transient and permanent blindness and significant partial vision loss have been reported with the use of 5- HT1 agonists. Visual disorders may also be part of a migraine attack.

Increase in Blood Pressure:

As with other 5-HT1 agonists, significant elevations in systemic blood pressure have been reported on rare occasions with ZOMIG Tablet use, in patients with and without a history of hypertension; very rarely these increases in blood pressure have been associated with significant clinical events. Zolmitriptan is contraindicated in patients with uncontrolled hypertension. In volunteers, an increase of 1 and 5 mm Hg in the systolic and diastolic blood pressure, respectively, was seen at 5 mg. In the headache trials, vital signs were measured only in the small inpatient study and no effect on blood pressure was seen. In a study of patients with moderate to severe liver disease, 7 of 27 experienced 20 to 80 mm Hg elevations in systolic and/or diastolic blood pressure after a dose of 10 mg of zolmitriptan (see CONTRAINDICATIONS).

An 18% increase in mean pulmonary artery pressure was seen following dosing with another 5-HT1 agonist in a study evaluating subjects undergoing cardiac catheterization.

PRECAUTIONS

General:

As with other 5-HT1B/1D agonists, sensations of tightness, pain, pressure, and heaviness have been reported after treatment with ZOMIG Tablets in the precordium, throat, neck, and jaw. Because zolmitriptan may cause coronary artery vasospasm, patients who experience signs or symptoms suggestive of angina following dosing should be evaluated for the presence of CAD or a predisposition to Prinzmetal’s variant angina before receiving additional doses of medication, and should be monitored electrocardiographically if dosing is resumed and similar symptoms recur. Similarly, patients who experience other symptoms or signs suggestive of decreased arterial flow, such as ischemic bowel syndrome or Raynaud’s syndrome following the use of any 5-HT1 agonist are candidates for further evaluation. (see CONTRAINDICATIONS and WARNINGS.)

Zolmitriptan should also be administered with caution to patients with diseases that may alter the absorption, metabolism, or excretion of drugs, such as impaired hepatic function (see CLINICAL PHARMACOLOGY).

For a given attack, if a patient does not respond to the first dose of zolmitriptan, the diagnosis of migraine headache should be reconsidered before administration of a second dose.

Binding to Melanin-Containing Tissues:

When pigmented rats were given a single oral dose of 10 mg/kg of radiolabeled zolmitriptan, the radioactivity in the eye after 7 days, the latest time point examined, was still 75% of the value measured after 4 hours. This suggests that zolmitriptan and/or its metabolites may bind to the melanin of the eye. Because there could be accumulation in melanin rich tissues over time, this raises the possibility that zolmitriptan could cause toxicity in these tissues after extended use. However, no effects on the retina related to treatment with zolmitriptan were noted in any of the toxicity studies. Although no systematic monitoring of ophthalmologic function was undertaken in clinical trials, and no specific recommendations for ophthalmologic monitoring are offered, prescribers should be aware of the possibility of long-term ophthalmologic effects.

Phenylketonurics:

Phenylketonuric patients should be informed that ZOMIG-ZMT contain phenylalanine (a component of aspartame). Each 2.5 mg orally disintegrating tablet contains 2.81 mg phenylalanine. Each 5 mg orally disintegrating tablet contains 5.62 mg phenylalanine.

Information for Patients

See PATIENT INFORMATION at the end of this labeling for the text of the separate leaflet provided for patients.

ZOMIG-ZMT Orally Disintegrating Tablets

The orally disintegrating tablet is packaged in a blister. Patients should be instructed not to remove the tablet from the blister until just prior to dosing. The blister pack should then be peeled open, and the orally disintegrating tablet placed on the tongue, where it will dissolve and be swallowed with the saliva.

Patients should be cautioned about the risk of serotonin syndrome with the use of ZOMIG or other triptans, especially during combined use with selective serotonin reuptake inhibitors (SSRIs) or serotonin norepinephrine reuptake inhibitors (SNRIs).

Laboratory Tests:

No monitoring of specific laboratory tests is recommended.

Drug Interactions

Ergot-containing drugs have been reported to cause prolonged vasospastic reactions. Because there is a theoretical basis that these effects may be additive, use of ergotamine-containing or ergot-type medications (like dihydroergotamine or methysergide) and zolmitriptan within 24 hours of each other should be avoided (see CONTRAINDICATIONS).

MAO-A inhibitors increase the systemic exposure of zolmitriptan. Therefore, the use of zolmitriptan in patients receiving MAO-A inhibitors is contraindicated (see CLINICAL PHARMACOLOGYand CONTRAINDICATIONS).

Concomitant use of other 5-HT1B/1D agonists within 24 hours of ZOMIG treatment is not recommended. (see CONTRAINDICATIONS).

Following administration of cimetidine, the half-life and AUC of zolmitriptan and its active metabolites were approximately doubled (see CLINICAL PHARMACOLOGY).

Selective Serotonin Reuptake Inhibitors/Serotonin Norepinephrine Reuptake Inhibitors and Serotonin Syndrome: Cases of life-threatening serotonin syndrome have been reported during combined use of selective serotonin reuptake inhibitors (SSRIs) or serotonin norepinephrine reuptake inhibitors (SNRIs) and triptans (See WARNINGS).

Drug/Laboratory Test Interactions:

Zolmitriptan is not known to interfere with commonly employed clinical laboratory tests.

Carcinogenesis:

Carcinogenicity studies by oral gavage were carried out in mice and rats at doses up to 400 mg/kg/day. Mice were dosed for 85 weeks (males) and 92 weeks (females). The exposure (plasma AUC of parent drug) at the highest dose level was approximately 800 times that seen in humans after a single 10 mg dose (the maximum recommended total daily dose). There was no effect of zolmitriptan on tumor incidence. Control, low dose, and middle dose rats were dosed for 104-105 weeks; the high dose group was sacrificed after 101 weeks (males) and 86 weeks (females) due to excess mortality. Aside from an increase in the incidence of thyroid follicular cell hyperplasia and thyroid follicular cell adenomas seen in male rats receiving 400 mg/kg/day, an exposure approximately 3000 times that seen in humans after dosing with 10 mg, no tumors were noted.

Mutagenesis:

Zolmitriptan was mutagenic in an Ames test, in 2 of 5 strains of S. typhimurium tested, in the presence of, but not in the absence of, metabolic activation. It was not mutagenic in an in vitro mammalian gene cell mutation (CHO/HGPRT) assay. Zolmitriptan was clastogenic in an in vitro human lymphocyte assay both in the absence of and the presence of metabolic activation; it was not clastogenic in an in vivo mouse micronucleus assay. It was also not genotoxic in an unscheduled DNA synthesis study.

Impairment of Fertility:

Studies of male and female rats administered zolmitriptan prior to and during mating and up to implantation have shown no impairment of fertility at doses up to 400 mg/kg/day. Exposure at this dose was approximately 3000 times exposure at the maximum recommended human dose of 10 mg/day.

Pregnancy:

Pregnancy Category C:

There are no adequate and well controlled studies in pregnant women; therefore, zolmitriptan should be used during pregnancy only if the potential benefit justifies the potential risk to the fetus.

In reproductive toxicity studies in rats and rabbits, oral administration of zolmitriptan to pregnant animals was associated with embryolethality and fetal abnormalities. When pregnant rats were administered oral zolmitriptan during the period of organogenesis at doses of 100, 400, and 1200 mg/kg/day, there was a dose-related increase in embryolethality which became statistically significant at the high dose. The maternal plasma exposures at these doses were approximately 280, 1100, and 5000 times the exposure in humans receiving the maximum recommended total daily dose of 10 mg. The high dose was maternally toxic, as evidenced by a decreased maternal body weight gain during gestation. In a similar study in rabbits, embryolethality was increased at the maternally toxic doses of 10 and 30 mg/kg/day (maternal plasma exposures equivalent to 11 and 42 times exposure in humans receiving the maximum recommended total daily dose of 10 mg), and increased incidences of fetal malformations (fused sternebrae, rib anomalies) and variations (major blood vessel variations, irregular ossification pattern of ribs) were observed at 30 mg/kg/day. Three mg/kg/day was a no effect dose (equivalent to human exposure at a dose of 10 mg). When female rats were given zolmitriptan during gestation, parturition, and lactation, an increased incidence of hydronephrosis was found in the offspring at the maternally toxic dose of 400 mg/kg/day (1100 times human exposure).

Nursing Mothers:

It is not known whether zolmitriptan is excreted in human milk. Because many drugs are excreted in human milk, caution should be exercised when zolmitriptan is administered to a nursing woman. Lactating rats dosed with zolmitriptan had milk levels equivalent to maternal plasma levels at 1 hour and 4 times higher than plasma levels at 4 hours.

Pediatric Use:

Safety and effectiveness of ZOMIG Tablets in pediatric patients have not been established. Therefore, ZOMIG is not recommended for use in patients under 18 years of age.

One randomized, placebo-controlled clinical trial evaluating zolmitriptan tablets (2.5, 5 and 10 mg) in pediatric patients aged 12-17 years evaluated a total of 696 adolescent migraineurs. This study did not establish the efficacy of zolmitriptan compared to placebo in the treatment of migraine in adolescents. Adverse events observed were similar in nature and frequency to those reported in clinical trials in adults.

Postmarketing experience with ZOMIG and other triptans includes a limited number of reports that describe pediatric patients who have experienced clinically serious adverse events that are similar in nature to those reported rarely in adults.

Geriatric Use:

Although the pharmacokinetic disposition of the drug in the elderly is similar to that seen in younger adults, there is no information about the safety and effectiveness of zolmitriptan in this population because patients over age 65 were excluded from the controlled clinical trials. (see CLINICAL PHARMACOLOGY: Special Populations)

ADVERSE REACTIONS:

Serious cardiac events, including myocardial infarction, have occurred following the use of ZOMIG Tablets. These events are extremely rare and most have been reported in patients with risk factors predictive of CAD. Events reported, in association with drugs of this class, have included coronary artery vasospasm, transient myocardial ischemia, myocardial infarction, ventricular tachycardia, and ventricular fibrillation (see CONTRAINDICATIONS, WARNINGS, and PRECAUTIONS).

Incidence in Controlled Clinical Trials:

Among 2,633 patients treated with ZOMIG Tablets in the active and placebo controlled trials, no patients withdrew for reasons related to adverse events, but as patients treated a single headache in these trials, the opportunity for discontinuation was limited. In a long-term, open label study where patients were allowed to treat multiple migraine attacks for up to 1 year, 8% (167 out of 2,058) withdrew from the trial because of adverse experience. The most common events were paresthesia, asthenia, nausea, dizziness, pain, chest or neck tightness or heaviness, somnolence, and warm sensation.

Table 2 lists the adverse events that occurred in ≥ 2% of the 2,074 patients in any one of the ZOMIG 1 mg, ZOMIG 2.5 mg or ZOMIG 5 mg Tablets dose groups of the controlled clinical trials. Only events that were more frequent in a ZOMIG Tablets group compared to the placebo groups are included. The events cited reflect experience gained under closely monitored conditions of clinical trials in a highly selected patient population. In actual clinical practice or in other clinical trials, these frequency estimates may not apply, as the conditions of use, reporting behavior, and the kinds of patients treated may differ.

Several of the adverse events appear dose related, notably paresthesia, sensation of heaviness or tightness in chest, neck, jaw, and throat, dizziness, somnolence, and possibly asthenia and nausea.

Table 2: Adverse Experience Incidence in Five Placebo-Controlled Migraine Clinical Trials: Events Reported By ≥ 2% Patients Treated With ZOMIG Tablets
Adverse Event Type | Placebo; (n=401) | ZOMIG; 1 mg; (n=163) | ZOMIG; 2.5 mg; (n=498) | ZOMIG; 5 mg; (n=1012)
ATYPICAL SENSATIONS | 6% | 12% | 12% | 18%
Hyperesthesia | 1% | 1% | 1% | 2%
Paresthesia (all types) | 2% | 5% | 7% | 9%
Sensation warm/cold | 4% | 6% | 5% | 7%
PAIN AND PRESSURE SENSATIONS | 7% | 13% | 14% | 22%
Chest - pain/tightness/pressure and/or heaviness | 1% | 2% | 3% | 4%
Neck/throat/jaw - pain/tightness/pressure | 3% | 4% | 7% | 10%
Heaviness other than chest or neck | 1% | 1% | 2% | 5%
Pain − location specified | 1% | 2% | 2% | 3%
Other − Pressure/tightness/heaviness | 0 | 2% | 2% | 2%
DIGESTIVE | 8% | 11% | 16% | 14%
Dry mouth | 2% | 5% | 3% | 3%
Dyspepsia | 1% | 3% | 2% | 1%
Dysphagia | 0% | 0% | 0% | 2%
Nausea | 4% | 4% | 9% | 6%
NEUROLOGICAL | 10% | 11% | 17% | 21%
Dizziness | 4% | 6% | 8% | 10%
Somnolence | 3% | 5% | 6% | 8%
Vertigo | 0% | 0% | 0% | 2%
OTHER
Asthenia | 3% | 5% | 3% | 9%
Palpitations | 1% | 0% | <1% | 2%
Myalgia | <1% | 1% | 1% | 2%
Myasthenia | <1% | 0% | 1% | 2%
Sweating | 1% | 0% | 2% | 3%

ZOMIG is generally well tolerated. Across all doses, most adverse reactions were mild and transient and did not lead to long-lasting effects. The incidence of adverse events in controlled clinical trials was not affected by gender, weight, or age of the patients; use of prophylactic medications; or presence of aura. There were insufficient data to assess the impact of race on the incidence of adverse events.

Other Events:

In the paragraphs that follow, the frequencies of less commonly reported adverse clinical events are presented. Because the reports include events observed in open and uncontrolled studies, the role of ZOMIG in their causation cannot be reliably determined. Furthermore, variability associated with adverse event reporting, the terminology used to describe adverse events, etc., limit the value of the quantitative frequency estimates provided. Event frequencies are calculated as the number of patients who used ZOMIG Tablets (n=4,027) and reported an event divided by the total number of patients exposed to ZOMIG Tablets. All reported events are included except those already listed in the previous table, those too general to be informative, and those not reasonably associated with the use of the drug. Events are further classified within body system categories and enumerated in order of decreasing frequency using the following definitions: infrequent adverse events are those occurring in 1/100 to 1/1,000 patients and rare adverse events are those occurring in fewer than 1/1,000 patients.

Atypical sensation: Infrequent was hyperesthesia.

General: Infrequent were allergy reaction, chills, facial edema, fever, malaise, and photosensitivity.

Cardiovascular: Infrequent were arrhythmias, hypertension, and syncope. Rare were bradycardia, extrasystoles, postural hypotension, QT prolongation, tachycardia, and thrombophlebitis.

Digestive: Infrequent were increased appetite, tongue edema, esophagitis, gastroenteritis, liver function abnormality, and thirst. Rare were anorexia, constipation, gastritis, hematemesis, pancreatitis, melena, and ulcer.

Hemic: Infrequent was ecchymosis. Rare were cyanosis, thrombocytopenia, eosinophilia, and leukopenia.

Metabolic: Infrequent was edema. Rare were hyperglycemia and alkaline phosphatase increased.

Musculoskeletal: Infrequent were back pain, leg cramps, and tenosynovitis. Rare were arthritis, asthenia, tetany, and twitching.

Neurological: Infrequent were agitation, anxiety, depression, emotional lability, and insomnia. Rare were akathisia, amnesia, apathy, ataxia, dystonia, euphoria, hallucinations, cerebral ischemia, hyperkinesia, hypotonia, hypertonia, and irritability.

Respiratory: Infrequent were bronchitis, bronchospasm, epistaxis, hiccup, laryngitis, and yawn. Rare were apnea and voice alteration.

Skin: Infrequent were pruritus, rash, and urticaria.

Special Senses: Infrequent were dry eye, eye pain, hyperacusis, ear pain, parosmia, and tinnitus. Rare were diplopia and lacrimation.

Urogenital: Infrequent were hematuria, cystitis, polyuria, urinary frequency, urinary urgency. Rare were miscarriage and dysmenorrhea.

The adverse experiences profile seen with ZOMIG-ZMT Tablets was similar to that seen with ZOMIG Tablets.

Postmarketing Experience with ZOMIG Tablets:

The following section enumerates potentially important adverse events that have occurred in clinical practice and which have been reported spontaneously to various surveillance systems. The events enumerated represent reports arising from both domestic and non-domestic use of oral zolmitriptan. The events enumerated include all except those already listed in the ADVERSE REACTIONS section above or those too general to be informative. Because the reports cite events reported spontaneously from worldwide postmarketing experience, frequency of events and the role of zolmitriptan in their causation cannot be reliably determined.

Cardiovascular:

Coronary artery vasospasm; transient myocardial ischemia, angina pectoris, and myocardial infarction.

Digestive:

Very rare gastrointestinal ischemic events including splenic infarction, ischemic colitis and gastrointestinal infarction or necrosis have been reported; these may present as bloody diarrhea or abdominal pain. (See WARNINGS.)

Neurological:

As with other acute migraine treatments including other 5HT1 agonists, there have been rare reports of headache.

General:

As with other 5-HT1B/1D agonists, there have been very rare reports of anaphylaxis or anaphylactoid reactions in patients receiving ZOMIG. There have been rare reports of hypersensitivity reactions, including angioedema.

Serotonin syndrome has also been reported during the postmarketing period (see WARNINGS and PRECAUTIONS).

DRUG ABUSE AND DEPENDENCE:

The abuse potential of ZOMIG has not been assessed in clinical trials.

OVERDOSAGE:

There is no experience with clinical overdose. Volunteers receiving single 50 mg oral doses of zolmitriptan commonly experienced sedation.

The elimination half-life of ZOMIG is 3 hours (see CLINICAL PHARMACOLOGY), and therefore monitoring of patients after overdose with ZOMIG should continue for at least 15 hours or while symptoms or signs persist.

There is no specific antidote to zolmitriptan. In cases of severe intoxication, intensive care procedures are recommended, including establishing and maintaining a patent airway, ensuring adequate oxygenation and ventilation, and monitoring and support of the cardiovascular system.

It is unknown what effect hemodialysis or peritoneal dialysis has on the plasma concentrations of zolmitriptan.

DOSAGE AND ADMINISTRATION:

ZOMIG Tablets

In controlled clinical trials, single doses of 1, 2.5 and 5 mg of ZOMIG Tablets were effective for the acute treatment of migraines in adults. A greater proportion of patients had headache response following a 2.5 or 5 mg dose than following a 1 mg dose (see Table 1). In the only direct comparison of 2.5 and 5 mg, there was little added benefit from the larger dose but side effects are generally increased at 5 mg (see Table 2). Patients should, therefore, be started on 2.5 mg or lower. A dose lower than 2.5 mg can be achieved by manually breaking the scored 2.5 mg tablet in half.

If the headache returns, the dose may be repeated after 2 hours, not to exceed 10 mg within a 24-hour period. Controlled trials have not adequately established the effectiveness of a second dose if the initial dose is ineffective.

The safety of treating an average of more than three headaches in a 30-day period has not been established.

ZOMIG-ZMT Orally Disintegrating Tablets

In a controlled clinical trial, a single dose of 2.5 mg of ZOMIG-ZMT Tablets was effective for the acute treatment of migraines in adults.

If the headache returns, the dose may be repeated after 2 hours, not to exceed 10 mg within a 24-hour period. Controlled trials have not adequately established the effectiveness of a second dose if the initial dose is ineffective.

The safety of treating an average of more than three headaches in a 30-day period has not been established.

Administration with liquid is not necessary. The orally disintegrating tablet is packaged in a blister. Patients should be instructed not to remove the tablet from the blister until just prior to dosing. The blister pack should then be peeled open, and the orally disintegrating tablet placed on the tongue, where it will dissolve and be swallowed with the saliva. It is not recommended to break the orally disintegrating tablet.

Hepatic Impairment:

Patients with moderate to severe hepatic impairment have decreased clearance of zolmitriptan and significant elevation in blood pressure was observed in some patients. Use of a low dose with blood pressure monitoring is recommended (see CLINICAL PHARMACOLOGY AND WARNINGS).

HOW SUPPLIED:

2.5 mg Tablets - Yellow, biconvex, round film-coated, scored tablets containing 2.5 mg of zolmitriptan identified with “ZOMIG” and “2.5” debossed on one side are supplied in cartons containing a blister pack of 6 tablets (NDC 0310-0210-20).

2.5 mg Orally Disintegrating Tablets - White, flat faced, uncoated, bevelled tablet containing 2.5 mg of zolmitriptan identified with a debossed “Z” on one side are supplied in cartons containing a blister pack of 6 tablets (NDC 0310-0209-20).

5 mg Tablets − Pink, biconvex, film-coated tablets containing 5 mg of zolmitriptan identified with “ZOMIG” and “5” debossed on one side are supplied in cartons containing a blister pack of 3 tablets (NDC 0310-0211-25).

5 mg Orally Disintegrating Tablets - White, flat faced, round, uncoated, bevelled tablet containing 5.0 mg of zolmitriptan identified with a debossed “Z” and “5” on one side and plain on the other are supplied in cartons containing a blister pack of 3 tablets (NDC 0310-0213-21).

Store both ZOMIG Tablets and ZOMIG-ZMT Tablets at controlled room temperature, 20-25°C (68-77°F) [see USP]. Protect from light and moisture.

PATIENT INFORMATION

The following wording is contained in a separate leaflet provided for patients.

Patient Information about ZOMIG (Zo-mig) for Migraines

Generic Name: zolmitriptan (zol-mi-trip-tan)

Information for the Consumer on ZOMIG (zolmitriptan) Tablets:

Please read this leaflet carefully before you take ZOMIG Tablets. This provides a summary of the information available on your medicine. Please do not throw away this leaflet until you have finished your medicine. You may need to read this leaflet again. This leaflet does not contain all the information on ZOMIG Tablets. For further information or advice, ask your doctor or pharmacist.

Information About Your Medicine:

The name of your medicine is ZOMIG Tablets. It can be obtained only by prescription from your doctor. The decision to use ZOMIG Tablets is one that you and your doctor should make jointly, taking into account your individual preferences and medical circumstances. If you have risk factors for heart disease (such as high blood pressure, high cholesterol, obesity, diabetes, smoking, strong family history of heart disease, or you are postmenopausal or a male over the age of 40), you should tell your doctor, who should evaluate you for heart disease in order to determine if ZOMIG Tablets are appropriate for you. This medicine was prescribed for you to treat your particular condition and should not be used by others or for any other condition.

1. The Purpose of Your Medicine: ZOMIG Tablets are intended to relieve your migraine, but not to prevent or reduce the number of attacks you experience. Use ZOMIG Tablets only to treat an actual migraine attack.
2. Important Questions to Consider Before Taking ZOMIG Tablets: If the answer to any of the following questions is YES or if you do not know the answer, then you must discuss it with your doctor before you use ZOMIG Tablets.
  - Do you have any chest pain, heart disease, shortness of breath, or irregular heartbeats? Have you had a heart attack?
  - Do you have risk factors for heart disease (such as high blood pressure, high cholesterol, obesity, diabetes, smoking, strong family history of heart disease, or you are postmenopausal or a male over the age of 40)?
  - Have you had a stroke or problems with your blood circulation?
  - Do you have high blood pressure?
  - Are you pregnant? Do you think you might be pregnant? Are you trying to become pregnant? Are you not using adequate contraception? Are you breast feeding an infant?
  - If you are taking ZOMIG-ZMT®, are you sensitive to phenylalanine (a component of the artificial sweetener aspartame)?
  - Have you ever had to stop taking this or any other medication because of an allergy or other problems?
  - Are you taking any other migraine medications, including 5-HT1 agonists (triptans) or migraine medications containing ergotamine, dihydroergotamine, or methysergide?
  - Are you taking selective serotonin reuptake inhibitors (SSRIs) or serotonin norepinephrine reuptake inhibitors (SNRIs), two types of drugs for depression or other disorders? Common SSRIs are CELEXA® (citalopram HBr), LEXAPRO® (escitalopram oxalate), PAXIL® (paroxetine), PROZAC® (fluoxetine), SYMBYAX® (olanzapine/fluoxetine), ZOLOFT® (sertraline), SARAFEM® (fluoxetine), and LUVOX® (fluvoxamine). Common SNRIs are CYMBALTA® (duloxetine) and EFFEXOR® (venlafaxine).
  - Are you taking cimetidine for gastrointestinal symptoms?
  - Have you had, or do you have, any disease of the liver or kidney?
  - Have you had, or do you have, epilepsy or seizures?
  - Is this headache different from your usual migraine attacks?
  Remember, if you answered YES to any of the above questions, then you must discuss it with your doctor.
3. The Use of ZOMIG Tablets During Pregnancy: Do not use ZOMIG Tablets if you are pregnant, think you might be pregnant, are trying to become pregnant, or are not using adequate contraception, unless you have discussed this with your doctor.
4. How to Use ZOMIG Tablets and ZOMIG-ZMT Orally Disintegrating Tablets: Adults should be started on a 2.5 mg dose or lower administered by mouth. A dose lower than 2.5 mg can be achieved by manually breaking the conventional film-coated, scored 2.5 mg tablet in half. It is not recommended to break the ZOMIG-ZMT Tablet. If your headache comes back after your initial dose, a second dose may be administered anytime after 2 hours of taking the dose. For any attack where you have no response to the first dose, do not take a second dose without first consulting with your doctor. Do not take more than a total of 10 mg of ZOMIG in any 24-hour period. Discard any unused tablets or its portion that have been removed from the blister packaging. Do not take ZOMIG with any other drug in the same class (triptans) within 24 hours or within 24 hours of taking ergotamine-type medications such as ergotamine, dihydroergotamine or methysergide to treat your migraine.
  Additionally for ZOMIG-ZMT Tablets, the blister pack should be peeled open and the orally disintegrating tablet placed on the tongue, where it will dissolve and be swallowed with the saliva.
5. Side Effects to Watch for:
  - Some patients experience pain or tightness in the chest or throat, including muscle aches and pains, when using ZOMIG. If this happens to you, then discuss it with your doctor before using any more ZOMIG. If the chest pain is severe or does not go away, call your doctor immediately. As with other drugs in this class (triptans), there have been very rare reports of heart attack occurring in patients with and without risk factors for heart and blood vessel disease.
  - Some people experience: alterations of heart rate; temporary increase in blood pressure; sudden and severe stomach pain. Call your doctor immediately if you have any of these symptoms after taking ZOMIG.
  - Shortness of breath; wheeziness; heart throbbing; swelling of eyelids, face, or lips; or a skin rash, skin lumps, or hives happens rarely. If it happens to you, then tell your doctor immediately. Do not take any more ZOMIG unless your doctor tells you to do so.
  - Some people may have feelings of dry mouth, tingling, heat, heaviness, or pressure after treatment with ZOMIG. A few people may feel drowsy, dizzy, tired, or sick. Tell your doctor immediately if you have symptoms that you do not understand.
  - Some people may have a reaction called serotonin syndrome, which can be life-threatening, when they use ZOMIG. In particular, this reaction may occur when they use ZOMIG together with certain types of antidepressants known as SSRIs or SNRIs. Symptoms may include confusion, hallucinations, fast heart beat, feeling faint, fever, sweating, muscle spasm, difficulty walking, and/or diarrhea. Call your doctor immediately if you have any of these symptoms after taking ZOMIG.
6. What To Do If An Overdose Is Taken: If you have taken more medication than you have been told, contact either your doctor, hospital emergency department, or nearest poison control center immediately.
7. Storing Your Medicine: Keep your medicine in a safe place where children cannot reach it. It may be harmful to children. Store your medication away from light and moisture, and at a controlled room temperature. If your medication has expired (the expiration date is printed on the treatment pack), throw it away as instructed. If your doctor decides to stop your treatment, do not keep any leftover medicine unless your doctor tells you to. Throw away your medicine as instructed. Be sure that discarded tablets are out of the reach of children.

ZOMIG and ZOMIG-ZMT are registered trademarks of the AstraZeneca group of companies.

Other brands mentioned are trademarks of their respective owners and are not trademarks of the AstraZeneca group of companies. The makers of these brands are not affiliated with AstraZeneca or its products.

© AstraZeneca 2007, 2008

ZOMIG®(zolmitriptan) Tablets

Manufactured for:

AstraZeneca Pharmaceuticals LP

Wilmington, Delaware 19850

By: IPR Pharmaceuticals, Inc.

Canóvanas, PR 00729

ZOMIG-ZMT® (zolmitriptan) Orally Disintegrating Tablets

Manufactured for:

AstraZeneca Pharmaceuticals LP

Wilmington, Delaware 19850

By: CIMA Labs, Inc.

Eden Prairie, Minnesota 55344

Rev 10/08 SIC 30086–05

PACKAGE LABEL.PRINCIPAL DISPLAY PANEL

NDC 68258-7103-03